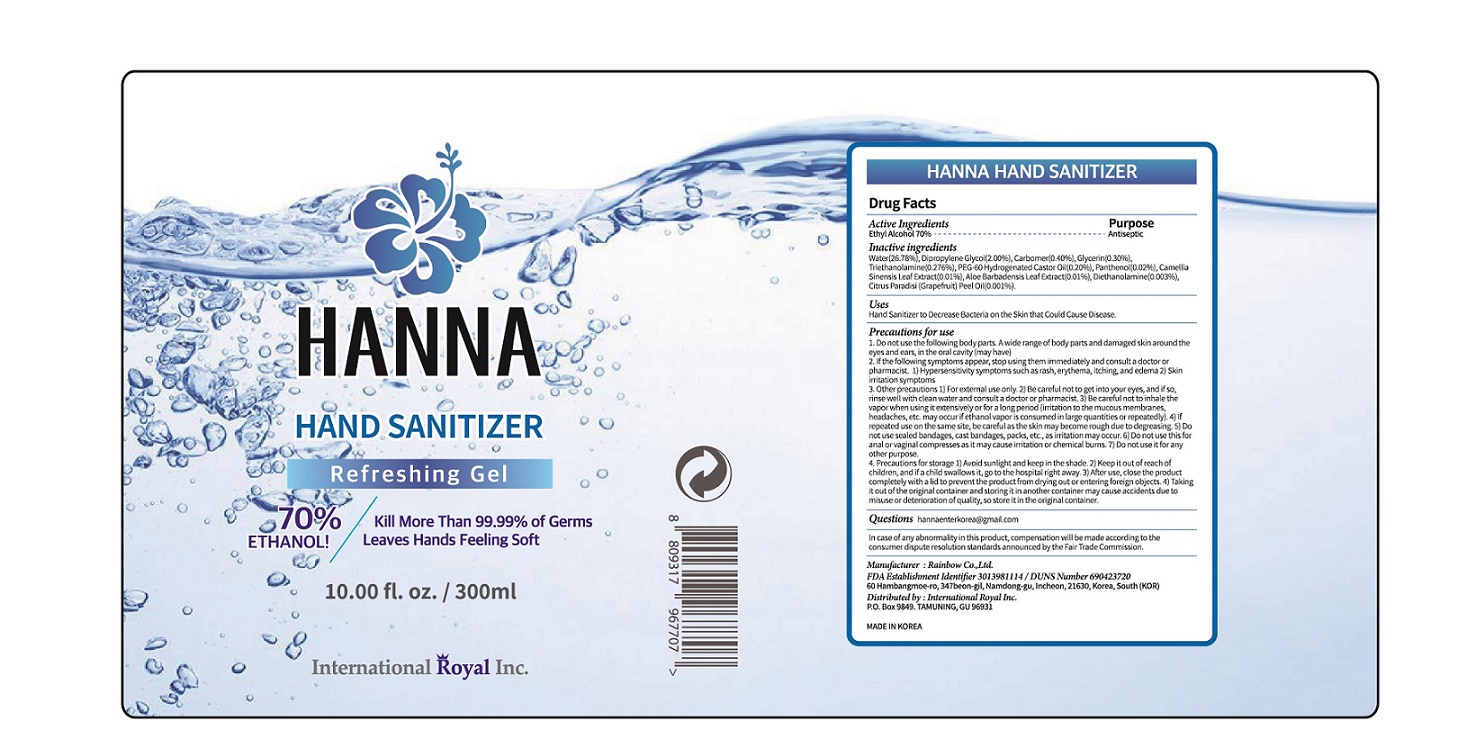 DRUG LABEL: HANNA Hand Sanitizer
NDC: 74247-0012 | Form: GEL
Manufacturer: Rainbow Co Ltd
Category: otc | Type: HUMAN OTC DRUG LABEL
Date: 20200725

ACTIVE INGREDIENTS: ALCOHOL 70 mL/100 mL
INACTIVE INGREDIENTS: GREEN TEA LEAF; GLYCERIN; GRAPEFRUIT PEEL; PEG-60 HYDROGENATED CASTOR OIL; DIETHANOLAMINE; PANTHENOL; DIPROPYLENE GLYCOL; ALOE VERA LEAF; CARBOMER 940; TROLAMINE; WATER

Drug Facts

ACTIVE INGREDIENT

alcohol

INACTIVE INGREDIENT

WATER
DIPROPYLENE GLYCOL
CARBOMER
GLYCERIN
TRIETHANOLAMINE
PEG-60 HYDROGENATED CASTOR OIL
PANTHENOL
CAMELLIA SINENSIS LEAF EXTRACT
ALOE 8AR8ADENSIS LEAF EXTRACT
DIETHANOLAMINE
CITRUS PARADIS! (GRAPEFRUIT) PEEL OIL

PURPOSE

Sterilization of hands and skin

KEEP OUT OF REACH OF THE CHILDREN

INDICATIONS AND USAGE

Apply to clean, dry hands. Apply sufficient amount to thoroughly wet all surfaces of hands and fingers. Rub onto hands until dry.

Supervise children in the use of this product.

WARNINGS

■ Flammable. Keep away from fire or flame.

■ For external use only.

■ Do not use in eyes.

■ lf swallowed, get medical help promptly.

■ Stop use, ask doctor lf irritation occurs.

■ Keep out of reach of children.

DOSAGE AND ADMINISTRATION

for external use only